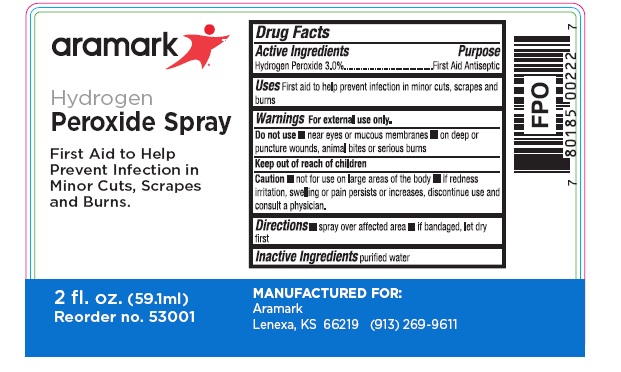 DRUG LABEL: aramark Hydrogen Peroxide
NDC: 81238-5400 | Form: SPRAY
Manufacturer: Western First Aid Safety DBA Aramark
Category: otc | Type: HUMAN OTC DRUG LABEL
Date: 20210524

ACTIVE INGREDIENTS: HYDROGEN PEROXIDE 3.0 mL/100 mL
INACTIVE INGREDIENTS: WATER

Aramark Hydrogen Proxide

Drug Facts

Active Ingredients

Hydrogen Peroxide 3.0%

Purpose

First Aid Antiseptic

Uses

First aid to help prevent infection in minor cuts, scrapes and burns

Warnings

For external use only.

Do not use

- near eyes or mucous membranes
- on deep or puncture wounds, animal bites, or serious burns

Keep out of reach of children.

Caution

- not for use on large areas of the body
- if redness, irritation, swelling or pain persists or increases, discontinue use and consult a physician

Directions

- spray over affected area
- if bandaged, let dry first

Inactive ingredients

purified water

Package Labeling

aramark

Hydrogen

Peroxide Spray

First Aid to Help
Prevent Infection in
Minor Cuts, Scrapes
and Burns.

2 fl. oz. (59.1ml)
Reorder no. 53001

MANUFACTURED FOR:
Aramark
Lenexa, KS 66219 (913) 269-9611

res